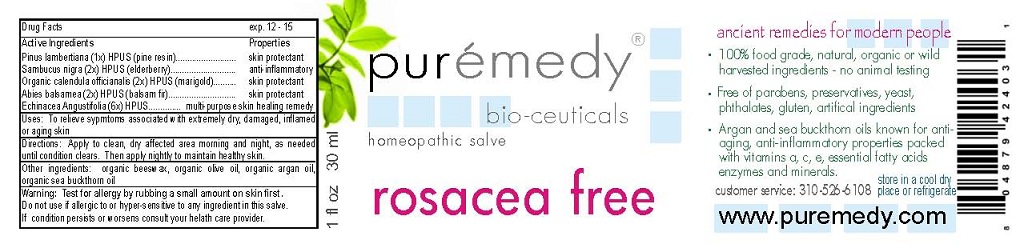 DRUG LABEL: ROSACEA FREE
NDC: 52810-602 | Form: SALVE
Manufacturer: PUREMEDY
Category: homeopathic | Type: HUMAN OTC DRUG LABEL
Date: 20211219

ACTIVE INGREDIENTS: SAMBUCUS NIGRA FLOWER 2 [hp_X]/100 mL; CALENDULA OFFICINALIS FLOWER 2 [hp_X]/100 mL; PINE NEEDLE OIL (PINUS SYLVESTRIS) 1 [hp_X]/100 mL; ABIES BALSAMEA LEAF OIL 2 [hp_X]/100 mL; ECHINACEA ANGUSTIFOLIA 6 [hp_X]/100 mL
INACTIVE INGREDIENTS: OLIVE OIL; ARGAN OIL; YELLOW WAX; HIPPOPHAE RHAMNOIDES WHOLE

ROSACEA FREE (52810-602)

ACTIVE INGREDIENTS

PINUS SILVESTRIS (1X) HPUS (PINE RESIN)

SAMBUCUS NIGRA (2X) HPUS (ELDERBERRY)

ORG. CALENDULA OFFICINALIS (2X) HPUS (MARIGOLD)

ABIES BALSAMEA (2X) HPUS (BALSAM FIR)

ECHINACEA ANGUSTIFOLIA (6X) HPUS

PURPOSE

PROPERTIES

SKIN PROTECTANT

ANTI-INFLAMMATORY

SKIN PROTECTANT

SKIN PROTECTANT

MULTI-PURPOSE SKIN HEALING REMEDY

INDICATIONS AND USAGE

USES: TO RELIEVE SYMPTOMS ASSOCIATED WITH EXTREMELY DRY, DAMAGED, INFLAMED OR AGING SKIN.

DOSAGE AND ADMINISTRATION

DIRECTIONS: APPLY TO CLEAN, DRY AFFECTED AREA MORNING AND NIGHT, AS NEEDED UNTIL CONDITION CLEARS. THEN APPLY NIGHTLY TO MAINTAIN HEALTHY SKIN.

INACTIVE INGREDIENT

OTHER INGREDIENTS: ORGANIC BEESWAX, ORGANIC OLIVE OIL, ORGANIC ARGAN OIL, ORGANIC SEA BUCKTHORN OIL

WARNINGS

WARNING: TEST FOR ALLERGY BY RUBBING A SMALL AMOUNT ON SKIN FIRST. DO NOT USE IF ALLERGIC TO OR HYPER-SENSITIVE TO ANY INGREDIENT IN THIS SALVE. IF CONDITION PERSISTS OR WORSENS CONSULT YOUR HEALTH CARE PROVIDER. (* = CERTIFIED ORGANIC INGREDIENTS)

KEEP OUT OF REACH OF CHILDREN.

QUESTIONS

CUSTOMER SERVICE 310-526-6108

OTHER SAFETY INFORMATION

STORE IN A COOL DRY PLACE OR REFRIGERATE